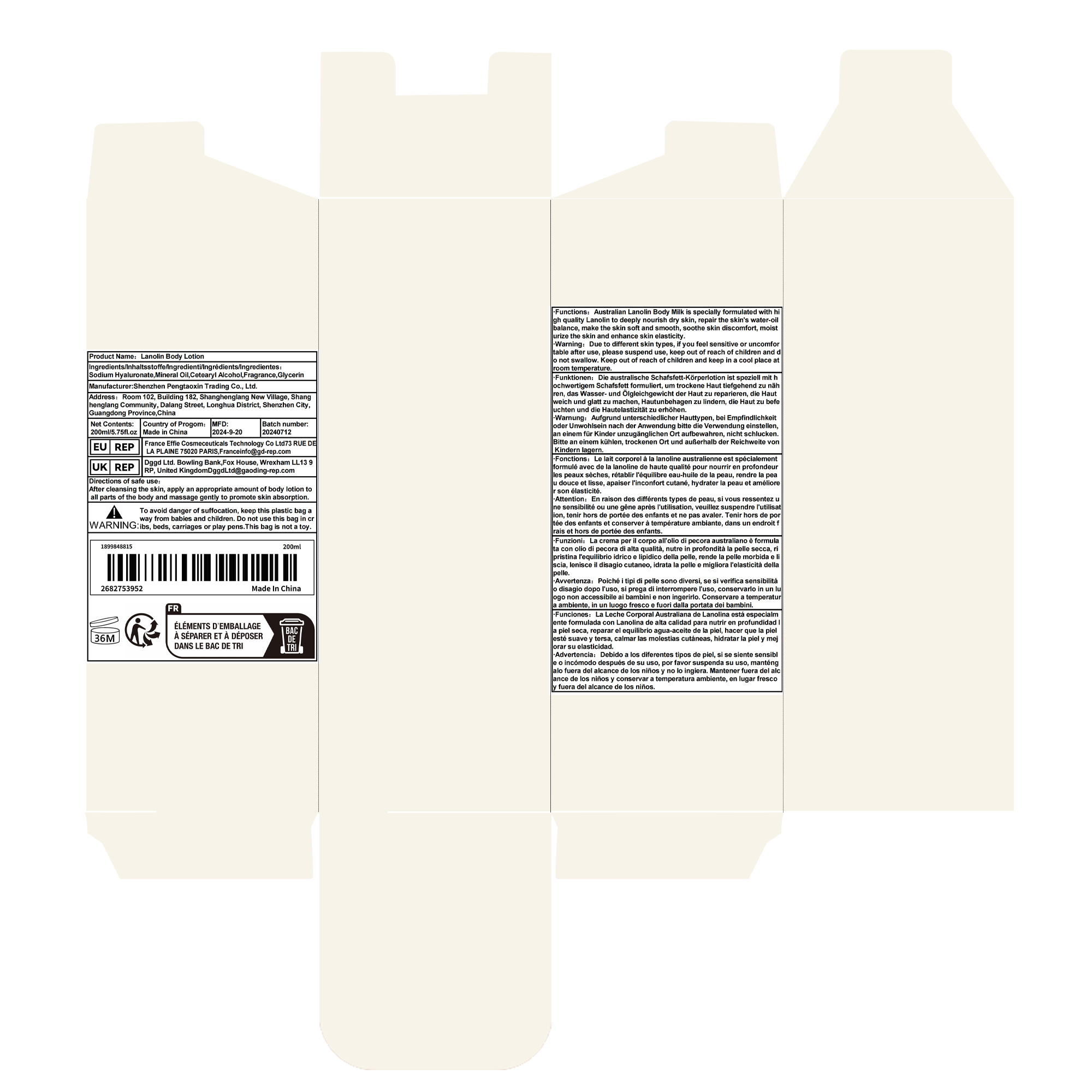 DRUG LABEL: LanolinBodyLotion
NDC: 84778-012 | Form: LOTION
Manufacturer: Guangzhou Yixin Cross-border E-commerce Co., Ltd.
Category: otc | Type: HUMAN OTC DRUG LABEL
Date: 20241013

ACTIVE INGREDIENTS: MINERAL OIL 20 g/200 mL
INACTIVE INGREDIENTS: FRAGRANCE 13576; CETOSTEARYL ALCOHOL; GLYCERIN; HYALURONATE SODIUM

Active ingredients

Mineral Oil 5%

Purpose

Deeply nourishes and moisturizes to help repair the skin barrier.

Uses

Body Milk is specially formulated with high quality Lanolin to deeply nourish dry skin, repair the skin's water-oil balance, make the skin soft and smooth, soothe the skin's discomfort, moisturize the skin and enhance the skin's elasticity.

Warnings

Due to different skin types, if you are sensitive or uncomfortable after use, please suspend use, please keep out of reach of children, do not swallow.

Dosage and administration

For external use only.

Do not use

Due to different skin types, if you are sensitive or uncomfortable after use, please suspend use, please keep out of reach of children, do not swallow.

When using section

After cleansing the skin, apply an appropriate amount of body lotion to all parts of the body and massage gently to promote skin absorption.

stop use

Due to different skin types, if you are sensitive or uncomfortable after use, please suspend use, please keep out of reach of children, do not swallow.

Keep out of reach of children.lf swallowed, get medical help or contacta Poison Control Center right away.

Inactive ingredients

Sodium Hyaluronate,Cetearyl Alcohol，Fragrance，Glycerin